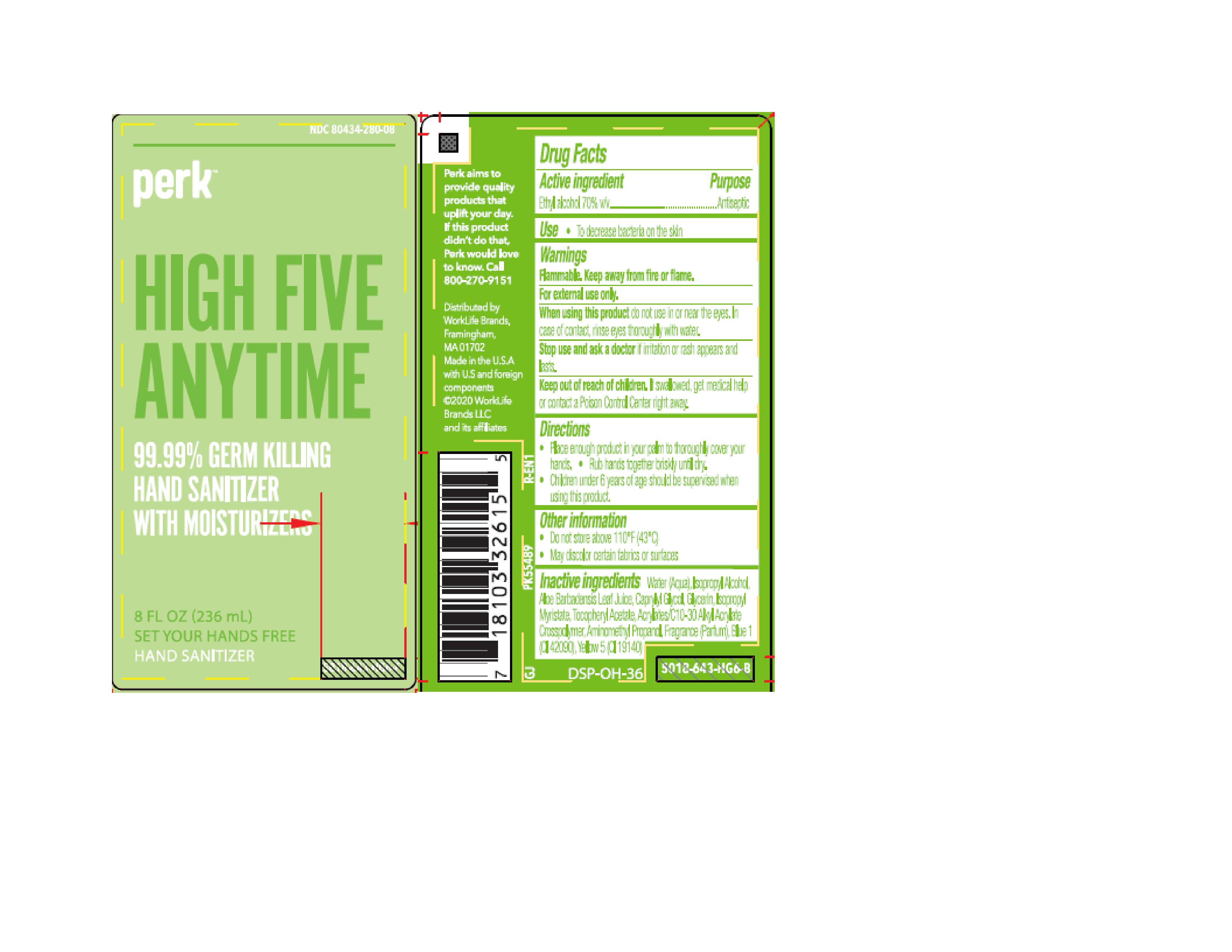 DRUG LABEL: Perk Hand Sanitizer with Moisturizers
NDC: 80434-281 | Form: GEL
Manufacturer: Worklifebrands LLC
Category: otc | Type: HUMAN OTC DRUG LABEL
Date: 20260113

ACTIVE INGREDIENTS: ALCOHOL 70 mL/100 mL
INACTIVE INGREDIENTS: WATER; ISOPROPYL ALCOHOL; GLYCERIN; ISOPROPYL MYRISTATE; .ALPHA.-TOCOPHEROL ACETATE, D-; CAPRYLYL GLYCOL; AMINOMETHYLPROPANOL; ALOE VERA LEAF; FD&C BLUE NO. 1; FD&C YELLOW NO. 5

Perk Hand Sanitizer with Moisturizers

Active ingredient

Ethyl alcohol 70% v/v

Purpose

Antiseptic

Use

To decrease bacteria on the skin

Warnings

Flammable. Keep away from fire or flame.

For external use only

WHEN USING

When using this productdo not use in or near the eyes. In case of contact, rinse eyes thoroughly with water.

Stop use and ask a doctor ifirritation or rash appears and lasts

Keep out of reach of children.If swallowed, get medical help or contact a Poison Control Center right away.

Directions

- Place enough product in your palm to thoroughly cover your hands
- Rub hands together briskly until dry
- Children under 6 years of age should be supervised when using this product.

Inactive ingredients

Water (Aqua), Isoproyl Alcohol, Aloe Barbadensis Leaf Juice, Caprylyl Glycol, Glycerin, Isopropyl Myristate, Tocopheryl Acetate, Acrylates/C10-30 Alkyl Acrylate Crosspolymer, Aminomethyl Propanol, Fragrance (Parfum), Blue 1 (CI 42090), Yellow 5 (CI 19140)